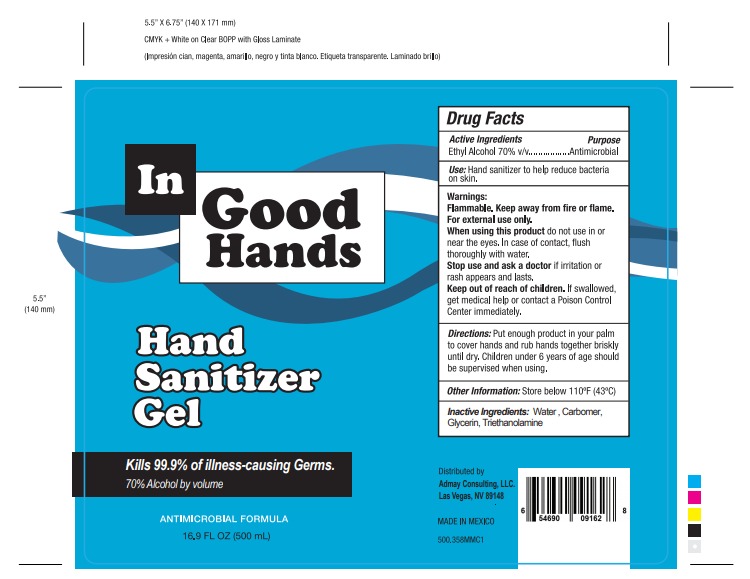 DRUG LABEL: IN GOOD HANDS
NDC: 76560-0002 | Form: GEL
Manufacturer: Plásticos las Palmas, S.A. de C.V.
Category: otc | Type: HUMAN OTC DRUG LABEL
Date: 20200607

ACTIVE INGREDIENTS: ALCOHOL 0.7 mL/1 mL
INACTIVE INGREDIENTS: CARBOMER 940 0.002 mL/1 mL; WATER 0.2585 mL/1 mL; TRIETHANOLAMINE CAPROYL GLUTAMATE 0.002 mL/1 mL; GLYCERIN 0.0375 mL/1 mL

IN GOOD HANDS HAND SANITIZER GEL

DOSAGE AND ADMINISTRATION

Place enough product on hands to cover all surfaces. Rub hands together until dry.

INDICATIONS AND USAGE

When using this product keep out of eyes, ears, and mouth. In case of contact with eyes, rinse eyes thoroughly with water.

INACTIVE INGREDIENTS

Inactive ingredients Water (Aqua), Glycerin, Carbomer, Triethanolamine

Keep out of reach of children. If swallowed, get medical help or contact a Poison Control Center right away.

PURPOSE

Purpose Antmicrobial

ACTIVE INGREDIENTS

Active ingredient. Ethyl Alcohol 70% v/v

WARNINGS AND PRECAUTIONS

Children under 6 years of age should be supervised when using

Store below 110°F (43°C)

WARNINGS

For external use only. Flammable. Keep away from heat or flame